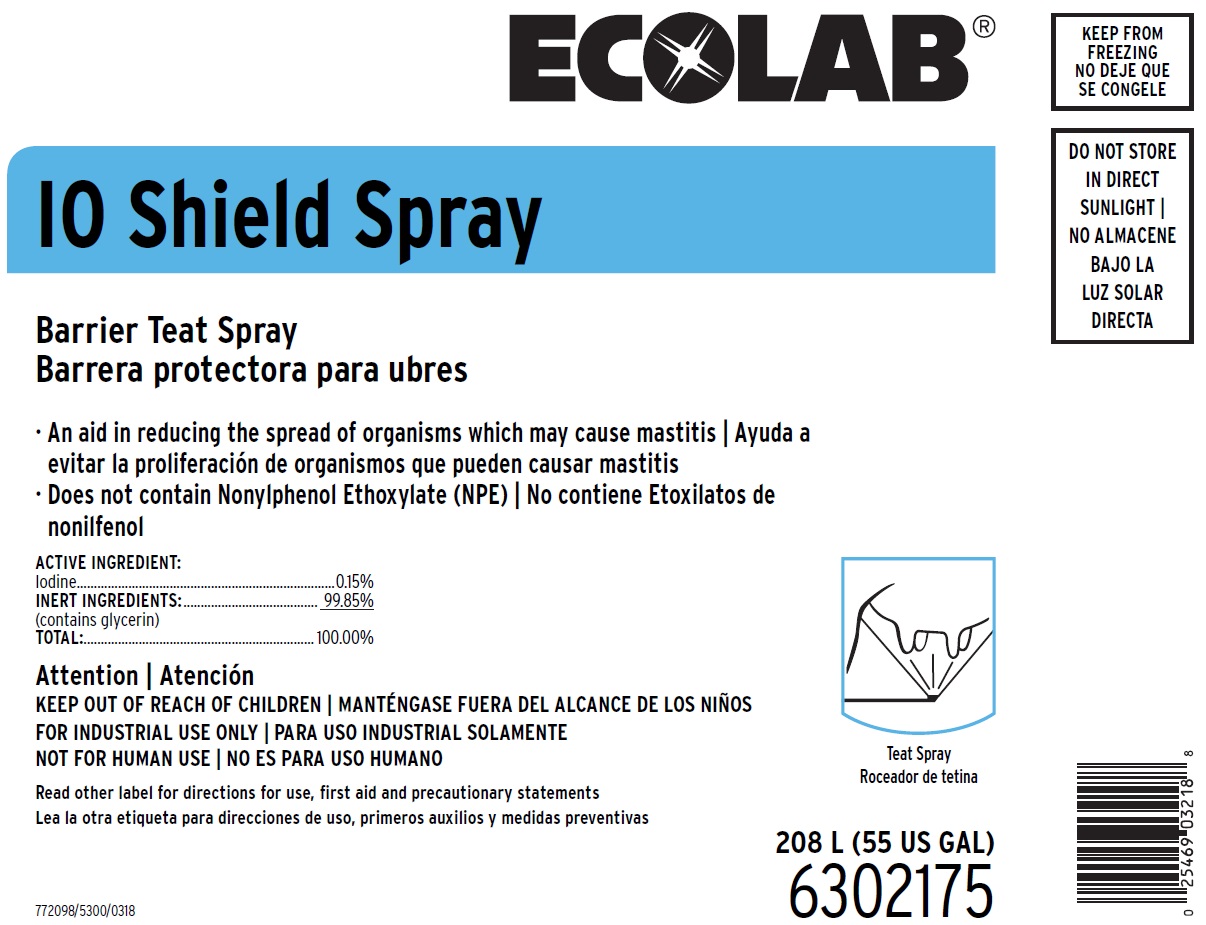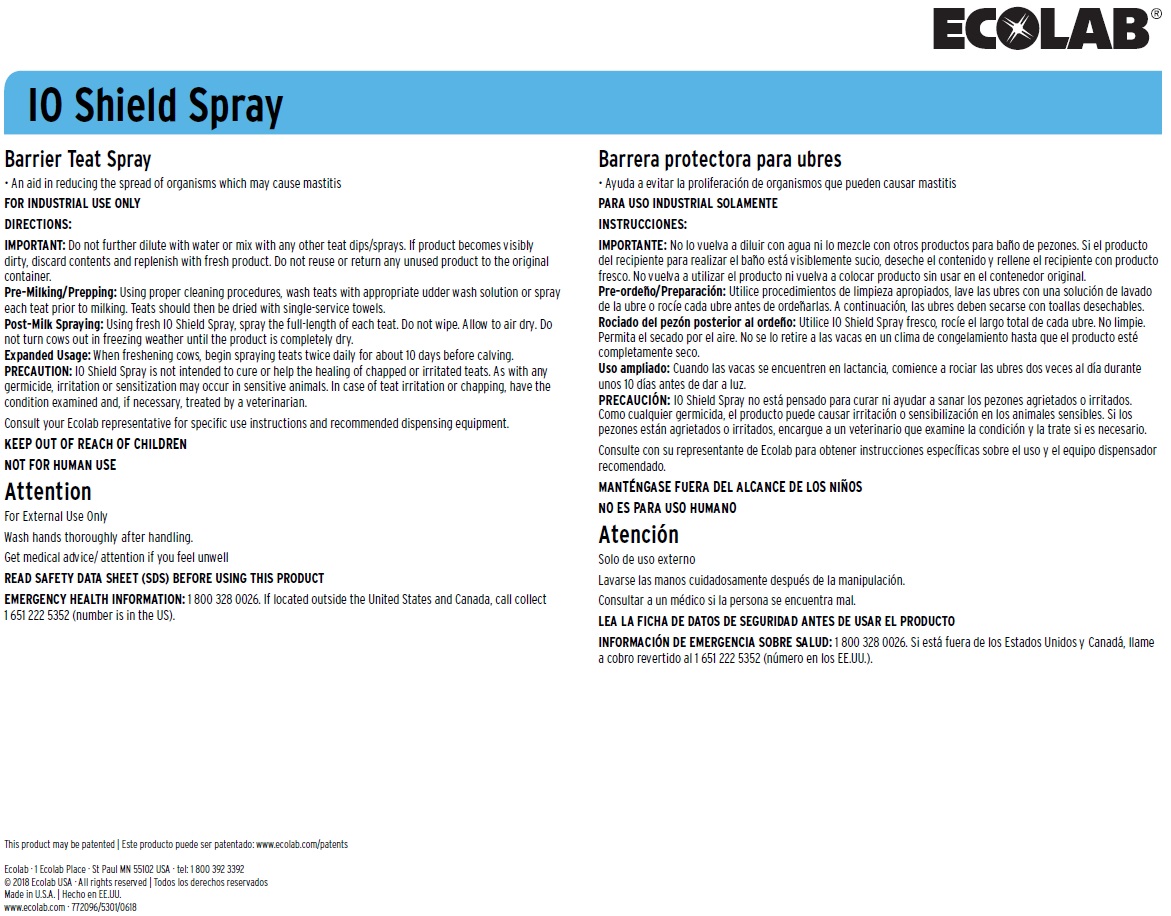 DRUG LABEL: IO Shield
NDC: 47593-588 | Form: SOLUTION
Manufacturer: Ecolab Inc.
Category: animal | Type: OTC ANIMAL DRUG LABEL
Date: 20251114

ACTIVE INGREDIENTS: IODINE 1.5 mg/1 mL
INACTIVE INGREDIENTS: GLYCERIN

KEEP OUT OF REACH OF CHILDREN
NOT FOR HUMAN USE
Attention
For External Use Only
Wash hands thoroughly after handling.
Get medical advice/ attention if you feel unwell

DIRECTIONS:
IMPORTANT: Do not further dilute with water or mix with any other teat dips/sprays. If product becomes visibly dirty, discard contents and replenish with fresh product. Do not reuse or return any unused product to the original container.
Pre-Milking/Prepping: Using proper cleaning procedures, wash teats with appropriate udder wash solution or spray each teat prior to milking. Teats should then be dried with single-service towels.
Post-Milk Spraying: Using fresh IO Shield Spray, spray the full-length of each teat. Do not wipe. Allow to air dry. Do not turn cows out in freezing weather until the product is completely dry.
Expanded Usage: When freshening cows, begin spraying teats twice daily for about 10 days before calving.
PRECAUTION: IO Shield Spray is not intended to cure or help the healing of chapped or irritated teats. As with any germicide, irritation or sensitization may occur in sensitive animals. In case of teat irritation or chapping, have the condition examined and, if necessary, treated by a veterinarian.
Consult your Ecolab representative for specific use instructions and recommended dispensing equipment.

OTHER SAFETY INFORMATION

Read other label for directions for use, first aid and precautionary statements
READ SAFETY DATA SHEET (SDS) BEFORE USING THIS PRODUCT
EMERGENCY HEALTH INFORMATION: 1 800 328 0026. If located outside the United States and Canada, call collect 1 651 222 5352 (number is in the US).

PACKAGE LABEL

ECOLAB

IO Shield Spray

Barrier Teat Spray

ACTIVE INGREDIENTS:
Iodine....................................................0.15%
INERT INGREDIENTS:...........................99.85%
(contains glycerin)
TOTAL:............................................... 100.0%

208 L (55 US GAL)

772098/5300/0318

6302175

This product may be patented

Ecolab · 1 Ecolab Place · St Paul MN 55102 USA · tel: 1 800 392 3392

© 2018 Ecolab USA · All rights reserved

Made in U.S.A.

www.ecolab.com · 772096/5301/0618